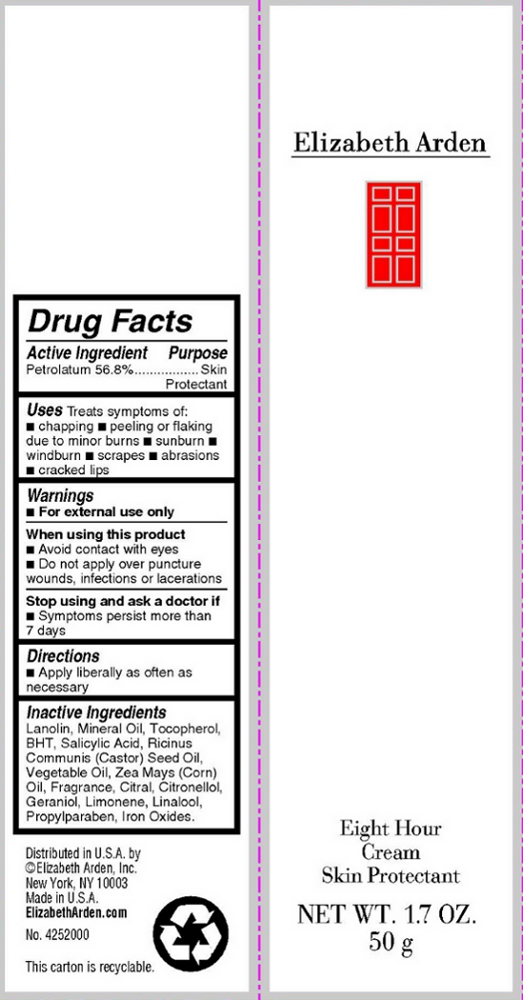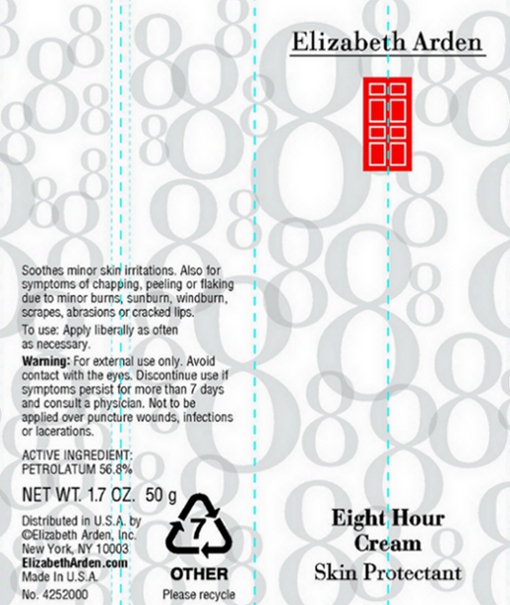 DRUG LABEL: Eight Hour Cream Skin Protectant
NDC: 67938-0105 | Form: LOTION
Manufacturer: Elizabeth Arden, Inc
Category: otc | Type: HUMAN OTC DRUG LABEL
Date: 20110114

ACTIVE INGREDIENTS: PETROLATUM 28.4 g/50 g
INACTIVE INGREDIENTS: LANOLIN; MINERAL OIL; SALICYLIC ACID; PROPYLPARABEN; CASTOR OIL; CORN OIL; ALPHA-TOCOPHEROL; BUTYLATED HYDROXYTOLUENE

BC0105

DESCRIPTION

(On Box) Uses: Treats symptoms of: chapping, peeling or flaking due to minor burns, sunburn, windburn, scrapes, abrasions, cracked lips.

(On Tube) Soothes minor skin irritations. Also for symptoms of chapping, peeling or flaking due to minor burns, sunburn, windburn, scrapes, abrasions or cracked lips.

INDICATIONS AND USAGE

To Use: Apply liberally as often as necessary.

WARNINGS

(On Box) Warnings: For external use only. When using this product: Avoid contact with eyes. Do not apply over puncture wounds, infections, or lacerations. Stop using and ask a doctor if: symptoms persist more than 7 days.

(On Tube) Warning: For external use only. Avoid contact with eyes. Discontinue use if symptoms persist more than 7 days and consult a physician. Not to be applied over puncture wounds, infections, or lacerations.

OTC - ACTIVE INGREDIENT

Active Ingredient: Petrolatum 56.8%.

INACTIVE INGREDIENT

Inactive Ingredients: Lanolin, Mineral Oil, Tocopherol, BHT, Salicylic Acid, Rincinus Communis (Castor) Seed Oil, Vegetable Oil, Zea Mays (Corn) Oil, Fragrance, Citral, Citronellol, Geraniol, Limonene, Linalool, Propylparaben, Iron Oxides.

DOSAGE & ADMINISTRATION

Apply liberally.

OTC - KEEP OUT OF REACH OF CHILDREN

Keep out of reach of children.

OTC - PURPOSE

Skin protectant.

OTC - WHEN USING

Avoid contact with eyes.